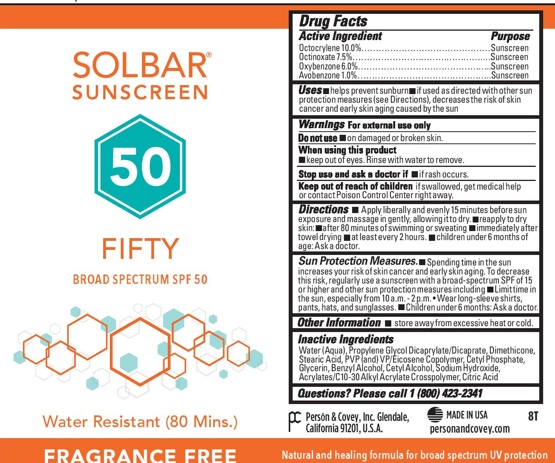 DRUG LABEL: Solbar Fifty SPF50
NDC: 0096-0741 | Form: CREAM
Manufacturer: Person and Covey
Category: otc | Type: HUMAN OTC DRUG LABEL
Date: 20251204

ACTIVE INGREDIENTS: OCTOCRYLENE 0.1 g/1 g; OCTINOXATE 0.08 g/1 g; OXYBENZONE 0.06 g/1 g; AVOBENZONE 0.011 g/1 g
INACTIVE INGREDIENTS: WATER; PROPYLENE GLYCOL DIETHYLHEXANOATE; DIMETHICONE; EICOSYL POVIDONE (2 EICOSYL BRANCHES/REPEAT); STEARIC ACID; CETYL PHOSPHATE; GLYCERIN; BENZYL ALCOHOL; CETYL ALCOHOL; CARBOMER 1342; TROLAMINE

Solbar Fifty SPF50

OTC - PURPOSE SECTION

Sun screen

INDICATIONS & USAGE SECTION

Helps prevent sunburn. If used as directed with other sun protection measures, decreases the risk of skin cancer and early skin aging caused by the sun.

DOSAGE & ADMINISTRATION SECTION

Apply liberally and evenly to all sun exposed areas of DRY skin 15 minutes before sun exposure. Reapply after 80 minutes of swimming or sweating and immediately after towel drying. Apply at least every 2 hours. For children under 6 months, ask a physician.

OTC - KEEP OUT OF REACH OF CHILDREN SECTION

Yes. If swallowed, get medical help or contact a Poison Control Center right away.

OTC - ACTIVE INGREDIENT SECTION

Octocrylene

Ethylhexyl Methoxycinnamate

Oxybenzone

Avobenzone

INACTIVE INGREDIENT SECTION

Purified Water

Propylene Glycol Diethylhexanoate

Dimethicone

PVP/Eicosene Copolymer

Stearic Acid

Cetyl Phosphate

Glycerin

Benzyl Alcohol

Cetyl Alcohol

Carbomer 1342

Triethanolamine

Warnings

For external use only. Do not use on damaged or broken skin. Keep out of eyes. Rinse eyes thoroughly with water to remove. Stop use and ask a physician if rash or irritation develops and lasts. Store away from excessive heat and direct sun.